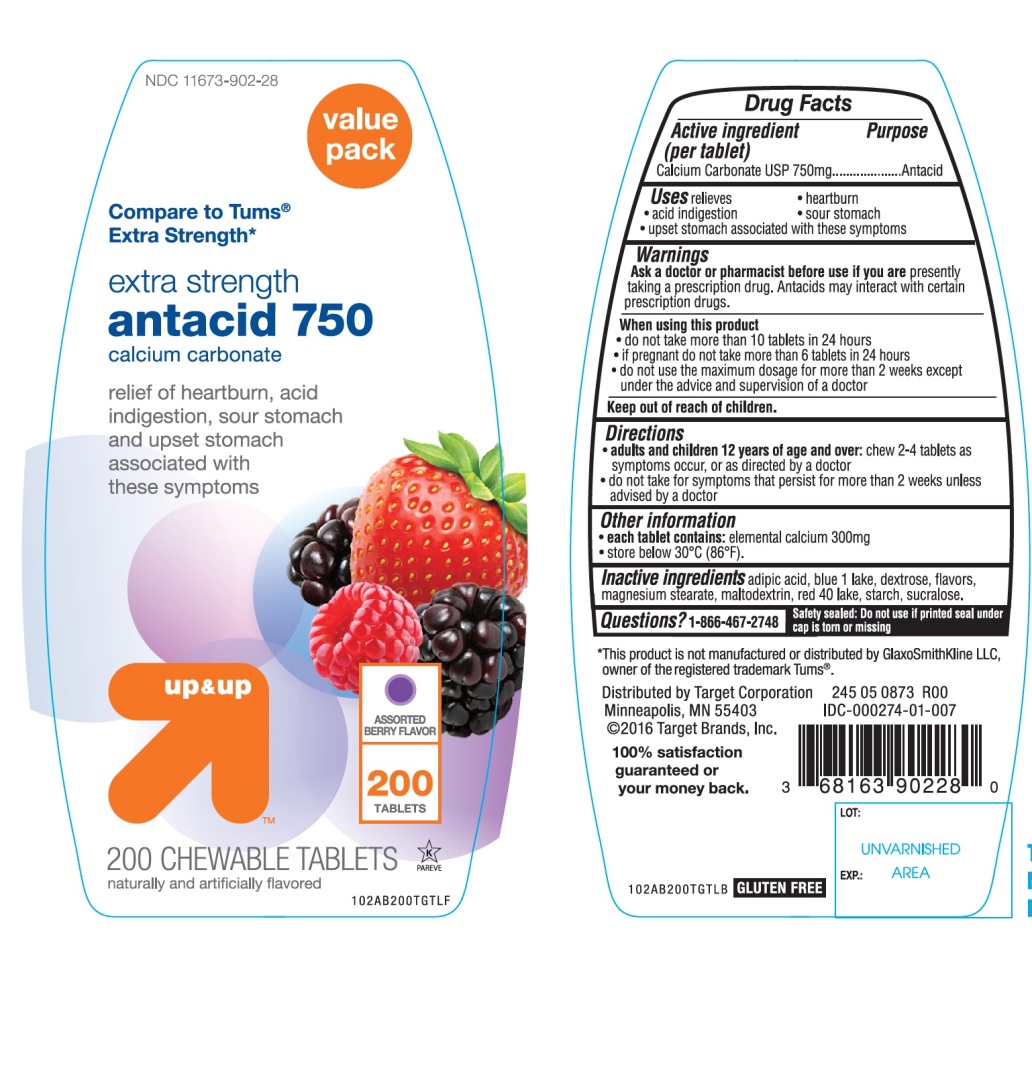 DRUG LABEL: up and up extra strength antacid 750

NDC: 11673-902 | Form: TABLET, CHEWABLE
Manufacturer: Target Corporation
Category: otc | Type: HUMAN OTC DRUG LABEL
Date: 20251104

ACTIVE INGREDIENTS: CALCIUM CARBONATE 750 mg/1 1
INACTIVE INGREDIENTS: ADIPIC ACID; FD&C BLUE NO. 1; DEXTROSE, UNSPECIFIED FORM; MAGNESIUM STEARATE; MALTODEXTRIN; FD&C RED NO. 40; STARCH, CORN; SUCRALOSE

up and up extra strength antacid 750

Active ingredient (per tablet)

Calcium Carbonate USP 750mg

Purpose

Antacid

Uses

relieves

• heartburn

• acid indigestion

• sour stomach

• upset stomach associated with these symptoms

Warnings

Ask a doctor or pharmacist before use if you arepresently taking a prescription drug. Antacids may interact with certain prescription drugs.

When using this product

- do not take more than 10 tablets in 24 hours
- if pregnant do not take more than 6 tablets in 24 hours
- do not use the maximum dosage for more than 2 weeks except under the advice and supervision of a doctor.

Directions

- adults and children 12 years of age and over:chew 2-4 tablets as symptoms occur, or as directed by a doctor
- do not take for symptoms that persist for more than 2 weeks unless advised by a doctor

Other information

• each tablet contains: elemental calcium 300mg

• store below 30°C (86°F)

Inactive ingredients

adipic acid, blue 1 lake, dextrose, flavors, magnesium stearate, maltodextrin, red 40 lake, starch, sucralose.

Questions?

1-866-467-2748

Safety sealed: Do not use if printed seal under cap is torn or missing

Package/Label Principal Display Panel

NDC 11673-902-28

Value Pack

Compare to Tums® Extra Strength*

extra strength

antacid 750

calcium carbonate

relief of heartburn, acid indigestion, sour stomach and upset stomach associated with these symptoms

ASSORTED BERRY FLAVOR

200 CHEWABLE TABLETS

naturally and artificially flavored

GLUTEN FREE

245 05 0873 R00

IDC-000274-01-007

Distributed by Target Corporation

Minneapolis, MN 55403

©2016 Target Brands, Inc.

*This product is not manufactured or distributed by GlaxoSmithKline LLC, owner of the registered trademark Tums®.

100% satisfaction guaranteed or your money back.